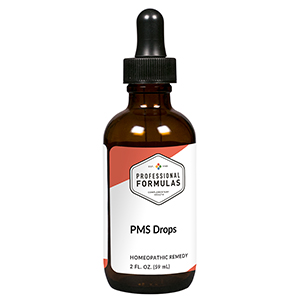 DRUG LABEL: PMS Drops
NDC: 63083-2124 | Form: LIQUID
Manufacturer: Professional Complementary Health Formulas
Category: homeopathic | Type: HUMAN OTC DRUG LABEL
Date: 20190815

ACTIVE INGREDIENTS: CHASTE TREE FRUIT 3 [hp_X]/59 mL; CAULOPHYLLUM THALICTROIDES ROOT 6 [hp_X]/59 mL; BLACK COHOSH 6 [hp_X]/59 mL; MAGNESIUM PHOSPHATE, DIBASIC TRIHYDRATE 6 [hp_X]/59 mL; BOS TAURUS PITUITARY GLAND, POSTERIOR 6 [hp_X]/59 mL; PULSATILLA MONTANA WHOLE 6 [hp_X]/59 mL; SEPIA OFFICINALIS JUICE 6 [hp_X]/59 mL; SPONGIA OFFICINALIS SKELETON, ROASTED 6 [hp_X]/59 mL; THYROID, UNSPECIFIED 6 [hp_X]/59 mL; VIBURNUM OPULUS BARK 6 [hp_X]/59 mL; LACHESIS MUTA VENOM 15 [hp_X]/59 mL; ESTROGENS, CONJUGATED 30 [hp_X]/59 mL; PROGESTERONE 30 [hp_X]/59 mL
INACTIVE INGREDIENTS: ALCOHOL; WATER

C124

ACTIVE INGREDIENTS

Agnus castus 3X
Caulophyllum thalictroides 6X
Cimicifuga racemosa 6X
Magnesia phosphorica 6X
Pituitary 6X
Pulsatilla 6X
Sepia 6X
Spongia tosta 6X
Thyroid 6X
Viburnum opulus 6X
Lachesis mutus 15X
Estrogen 30X
Progesterone 30X

QUESTIONS

Professional Formulas

PO Box 2034 Lake Oswego, OR 97035

INDICATIONS

For the temporary relief of cramping, lower abdominal or back pain, irritability, fatigue, or debility associated with pre-menstrual syndrome.*

PURPOSE

*Claims based on traditional homeopathic practice, not accepted medical evidence. Not FDA evaluated.

WARNINGS

In case of overdose, get medical help or contact a poison control center right away.

Keep out of the reach of children.

PREGNANCY OR BREAST FEEDING

If pregnant or breastfeeding, ask a healthcare professional before use.

DIRECTIONS

Place drops under tongue 30 minutes before/after meals. Adults and children 12 years and over: Take 10 drops up to 3 times per day for up to 6 weeks. For immediate onset of symptoms, take 10 to 15 drops every 15 minutes up to 3 hours. For less severe symptoms, take 10-15 drops hourly up to 8 hours. Consult a physician for use in children under 12 years of age.

OTHER INFORMATION

Tamper resistant. If seal is broken, do not use. After opening, close container tightly and store at room temperature away from heat.

INACTIVE INGREDIENTS

20% ethanol, purified water.

LABEL

Est 1985

Professional Formulas

Complementary Health

PMS Drops

Homeopathic Remedy

2 FL. OZ. (59 mL)